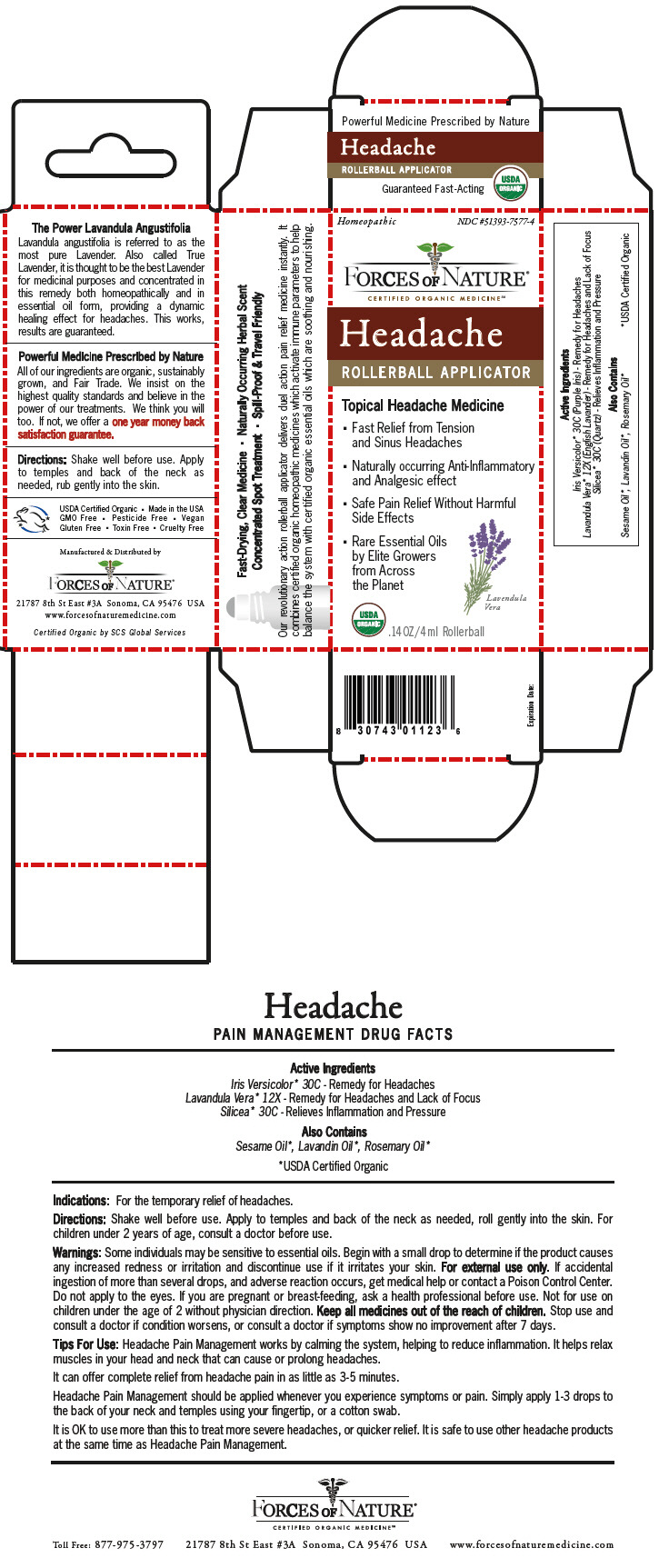 DRUG LABEL: Headache 
NDC: 51393-7577 | Form: SOLUTION/ DROPS
Manufacturer: Forces of Nature
Category: homeopathic | Type: HUMAN OTC DRUG LABEL
Date: 20221024

ACTIVE INGREDIENTS: Iris Versicolor Root 30 [hp_C]/1000 mL; Lavandula Angustifolia Subsp. Angustifolia Flowering Top 12 [hp_X]/1000 mL; Silicon Dioxide 30 [hp_C]/1000 mL
INACTIVE INGREDIENTS: Lavandin Oil; Rosemary Oil; Sesame Oil

Headache
Pain Management

DRUG FACTS

ACTIVE INGREDIENT

PURPOSE

Active Ingredients

Iris Versicolor [USDA Certified Organic] 30C - Remedy for Headaches

Lavandula Vera 12X - Remedy for Headaches and Lack of Focus

Silicea 30C - Relieves Inflammation and Pressure

Also Contains

Sesame Oil, Lavandin Oil, Rosemary Oil

Indications

For the temporary relief of headaches.

Directions

Shake well before use. Apply to temples and back of the neck as needed, roll gently into the skin. For children under 2 years of age, consult a doctor before use.

Warnings

Some individuals may be sensitive to essential oils. Begin with a small drop to determine if the product causes any increased redness or irritation and discontinue use if it irritates your skin. For external use only. If accidental ingestion of more than several drops, and adverse reaction occurs, get medical help or contact a Poison Control Center. Do not apply to the eyes. If you are pregnant or breast-feeding, ask a health professional before use. Not for use on children under the age of 2 without physician direction.

KEEP OUT OF REACH OF CHILDREN

Keep all medicines out of the reach of children. Stop use and consult a doctor if condition worsens, or consult a doctor if symptoms show no improvement after 7 days.

Tips For Use

Headache Pain Management works by calming the system, helping to reduce inflammation. It helps relax muscles in your head and neck that can cause or prolong headaches.

It can offer complete relief from headache pain in as little as 3-5 minutes.

Headache Pain Management should be applied whenever you experience symptoms or pain. Simply apply 1-3 drops to the back of your neck and temples using your fingertip, or a cotton swab.

It is OK to use more than this to treat more severe headaches, or quicker relief. It is safe to use other headache products at the same time as Headache Pain Management.

Manufactured & Distributed by:
FORCES OF NATURE®
21787 8th St East #3A Sonoma, CA 95476 USA

PRINCIPAL DISPLAY PANEL - 4 ml Bottle Carton

Homeopathic
NDC #51393-7577-4

FORCES OF NATURE®

CERTIFIED ORGANIC MEDICINE℠

Headache

ROLLERBALL APPLICATOR

Topical Headache Medicine

- Fast Relief from Tension
  and Sinus Headaches
- Naturally occurring Anti-Inflammatory
  and Analgesic effect
- Safe Pain Relief Without Harmful
  Side Effects
- Rare Essential Oils
  by Elite Growers
  from Across
  the Planet

Lavendula
Vera

USDA
ORGANIC

.14 OZ/4 ml Rollerball